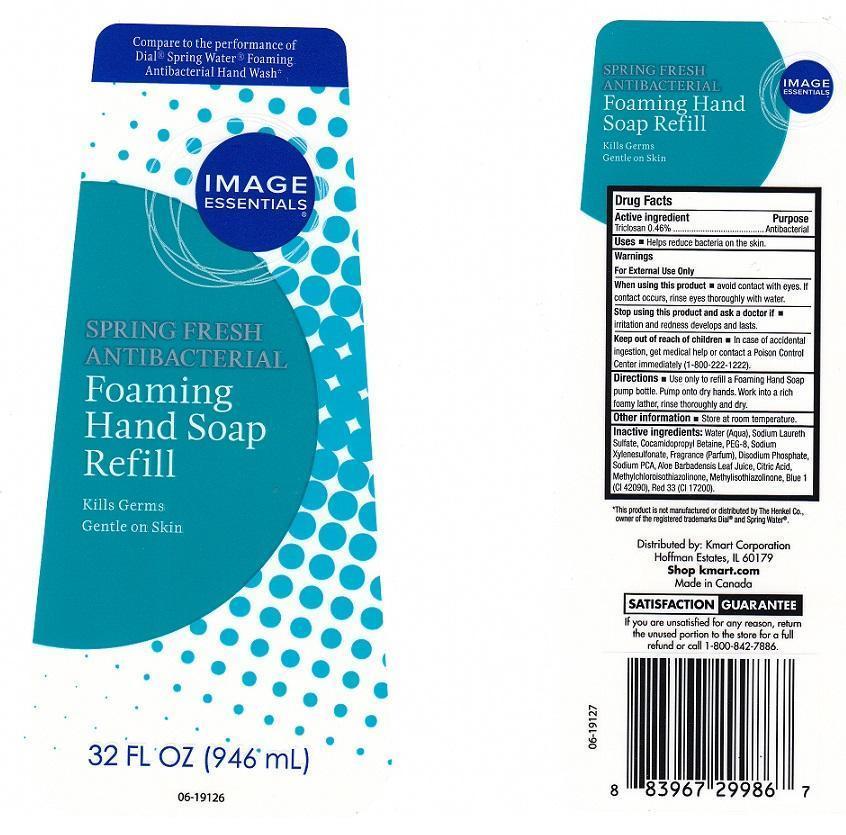 DRUG LABEL: IMAGE ESSENTIALS
NDC: 49738-101 | Form: LIQUID
Manufacturer: KMART CORPORATION
Category: otc | Type: HUMAN OTC DRUG LABEL
Date: 20131120

ACTIVE INGREDIENTS: TRICLOSAN 4.6 mg/1 mL
INACTIVE INGREDIENTS: WATER; SODIUM LAURETH SULFATE; COCAMIDOPROPYL BETAINE; POLYETHYLENE GLYCOL 400; SODIUM XYLENESULFONATE; SODIUM PHOSPHATE, DIBASIC ANHYDROUS; SODIUM PYRROLIDONE CARBOXYLATE; ALOE VERA LEAF; CITRIC ACID MONOHYDRATE; METHYLCHLOROISOTHIAZOLINONE; METHYLISOTHIAZOLINONE; FD&C BLUE NO. 1; D&C RED NO. 33

DRUG FACTS

ACTIVE INGREDIENT

TRICLOSAN 0.46%

PURPOSE

ANTIBACTERIAL

USES

HELPS REDUCE BACTERIA ON THE SKIN

WARNINGS

FOR EXTERNAL USE ONLY

WHEN USING THIS PRODUCT

AVOID CONTACT WITH EYES. IF CONTACT OCCURS, RINSE EYES THOROUGHLY WITH WATER

STOP USING THIS PRODUCT AND ASK A DOCTOR IF

IRRITATION AND REDNESS DEVELOPS AND LASTS

KEEP OUT OF REACH OF CHILDREN

IN CASE OF ACCIDENTAL INGESTION, GET MEDICAL HELP OR CONTACT A POISON CONTROL CENTER IMMEDIATELY

DIRECTIONS

USE ONLY TO REFILL A FOAMING HAND SOAP PUMP BOTTLE. PUMP ONTO DRY HANDS. WORK INTO A RICH FOAMY LATHER, RINSE THOROUGHLY AND DRY

OTHER INFORMATION

STORE AT ROOM TEMPERATURE

INACTIVE INGREDIENTS

WATER (AQUA), SODIUM LAURETH SULFATE, COCAMIDOPROPYL BETAINE, PEG-8, SODIUM XYLENESULFONATE, FRAGRANCE (PARFUM), DISODIUM PHOSPHATE, SODIUM PCA, ALOE BARBADENSIS LEAF JUICE, CITRIC ACID, METHYLCHLOROISOTHIAZOLINONE, METHYLISOTHIAZOLINONE, BLUE 1 (CI 42090), RED 33 (CI 17200)